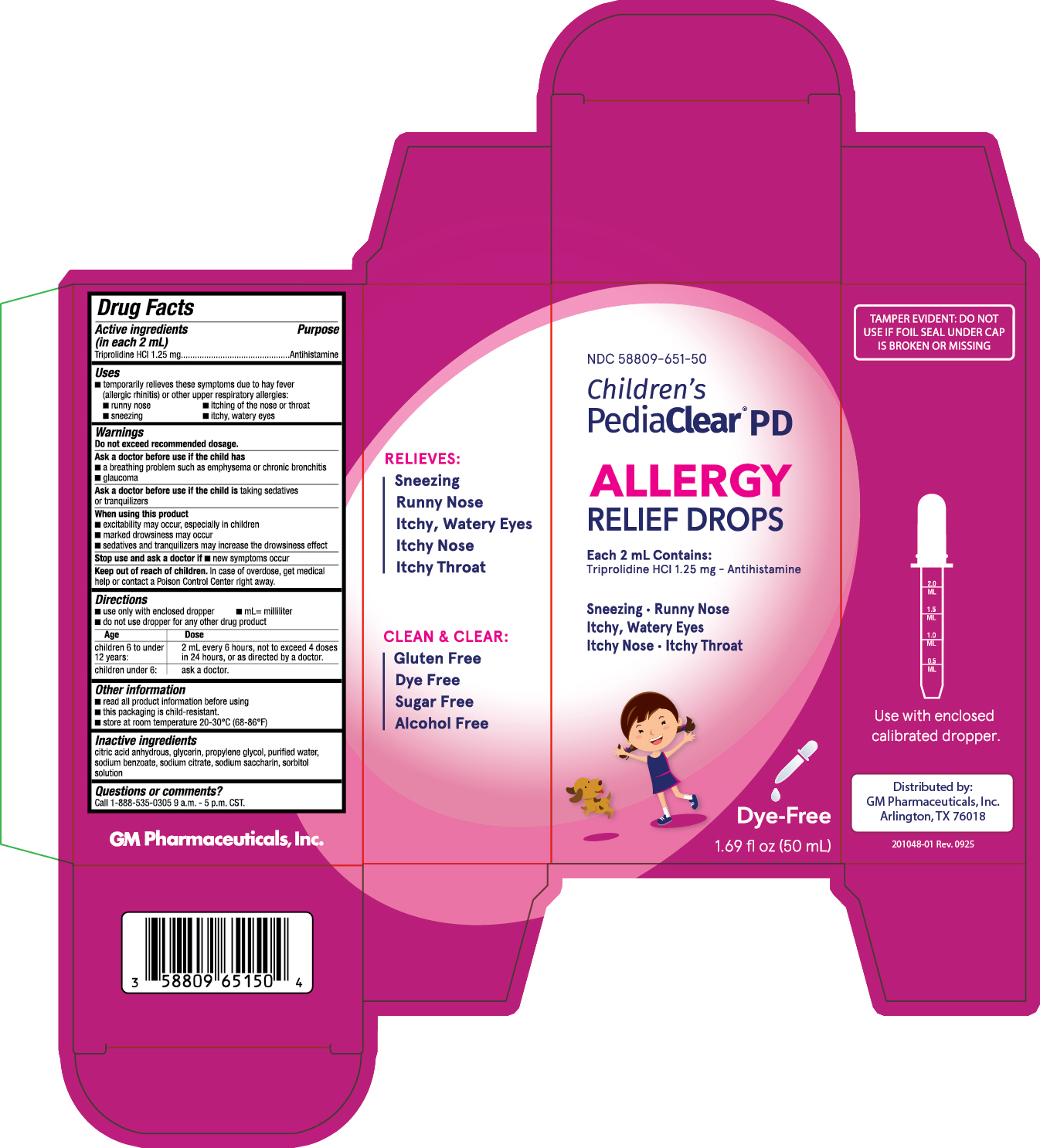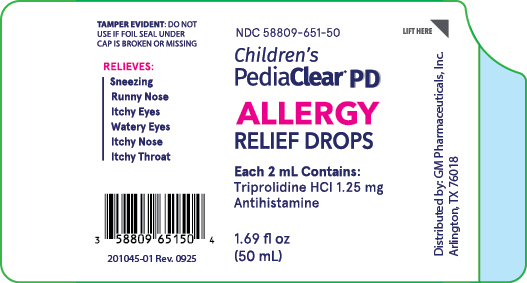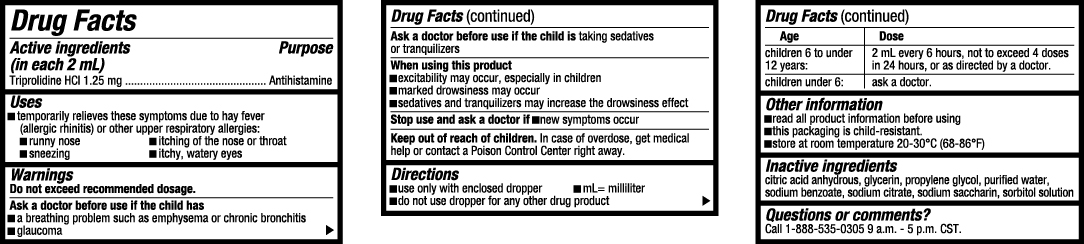 DRUG LABEL: Childrens PediaClear PD
NDC: 58809-651 | Form: LIQUID
Manufacturer: GM Pharmaceuticals, INC
Category: otc | Type: HUMAN OTC DRUG LABEL
Date: 20251003

ACTIVE INGREDIENTS: TRIPROLIDINE HYDROCHLORIDE 1.25 mg/2 mL
INACTIVE INGREDIENTS: ANHYDROUS CITRIC ACID; GLYCERIN; PROPYLENE GLYCOL; WATER; SODIUM BENZOATE; SODIUM CITRATE; SACCHARIN SODIUM; SORBITOL

Children's PediaClear PD

NDC 58809-651-50

Drug Facts

Active ingredients (in each 2 mL)

Triprolidine HCI 1.25 mg

Purpose

Antihistamine

Uses

■ temporarily relieves these symptoms due to hay fever

(allergic rhinitis) or other upper respiratory allergies:

■ runny nose ■ itching of the nose or throat

■ sneezing ■ itchy, watery eyes

Warnings

Do not exceed recommended dosage.

Ask a doctor before use if the child has

■ a breathing problem such as emphysema or chronic bronchitis

■ glaucoma

Ask a doctor before use if the child is

taking sedatives or tranquilizers

When using this product

■ excitability may occur, especially in children

■ marked drowsiness may occur

■ sedatives and tranquilizers may increase the drowsiness effect

Stop use and ask a doctor if

■ new symptoms occur

Keep out of reach of children.

In case of overdose, get medical help or contact a Poison Control Center right away.

Directions

■ use only with enclosed dropper ■ mL= milliliter

■ do not use dropper for any other drug product

Age | Dose
Children 6 to under 12 years: | 2 mL every 6 hours, not to exceed 4 doses in 24 hours, or as directed by a doctor.
Children under 6: | Ask a doctor.

Other information

■ read all product information before using

■ this packaging is child-resistant.

■ store at room temperature 20-30°C (68-86°F)

Inactive ingredients

citric acid anhydrous, glycerin, propylene glycol, purified water, sodium benzoate, sodium citrate, sodium saccharin, sorbitol solution

Questions or comments?

Call 1-888-535-0305 9 a.m. - 5 p.m. CST.

PRINCIPAL DISPLAY PANEL

NDC 58809-651-50
Children’s PediaClear PD Drops

1.69 fl oz (50 mL)

Children’s PediaClear PD Drops Label

Children’s PediaClear PD Drops Drug Facts

Children’s PediaClear PD Drops Carton